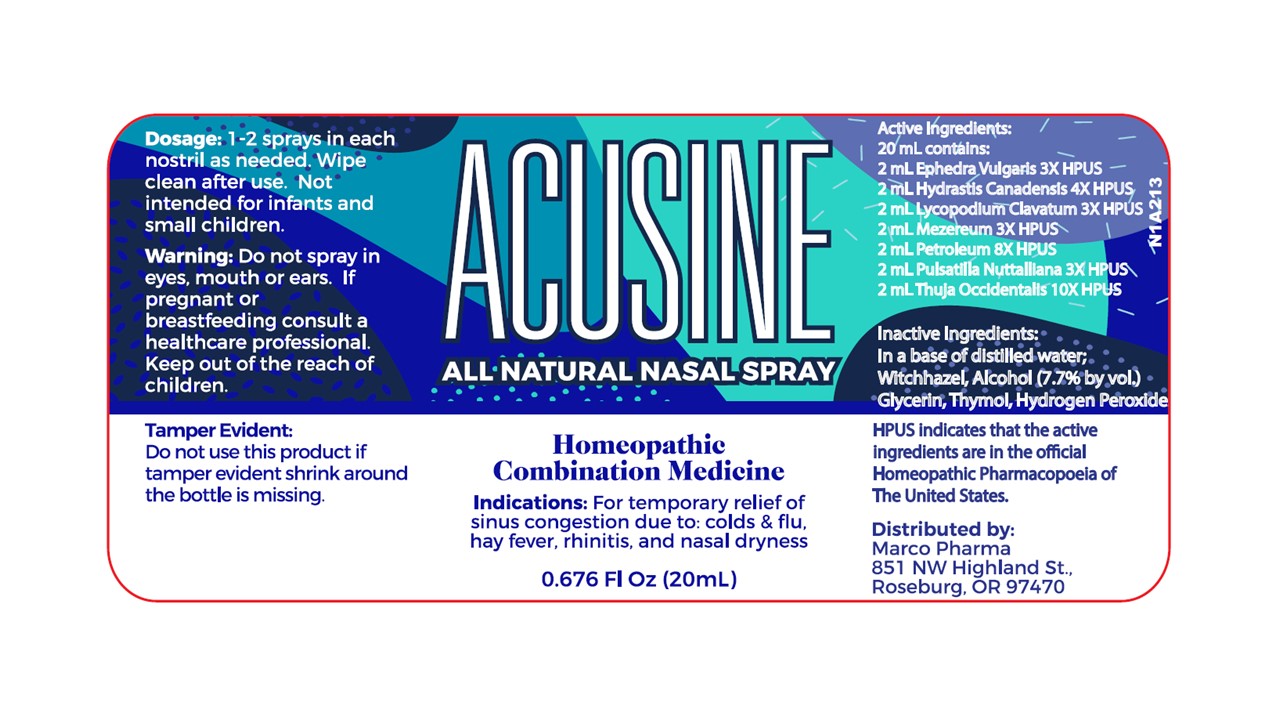 DRUG LABEL: Acusine
NDC: 60986-1040 | Form: SPRAY
Manufacturer: Marco Pharma International LLC
Category: homeopathic | Type: HUMAN OTC DRUG LABEL
Date: 20260112

ACTIVE INGREDIENTS: LYCOPODIUM CLAVATUM SPORE 3 [hp_X]/1 mL; PULSATILLA VULGARIS 3 [hp_X]/1 mL; DAPHNE MEZEREUM BARK 3 [hp_X]/1 mL; KEROSENE 8 [hp_X]/1 mL; THUJA OCCIDENTALIS LEAFY TWIG 10 [hp_X]/1 mL; EPHEDRA DISTACHYA FLOWERING TWIG 3 [hp_X]/1 mL; GOLDENSEAL 4 [hp_X]/1 mL
INACTIVE INGREDIENTS: HAMAMELIS VIRGINIANA TOP WATER; WATER; GLYCERIN; THYMOL; ALCOHOL

Acusine

ACTIVE INGREDIENT

Hydrastis Canadensis 4xHPUS

Lycopodium Clavatum 3xHPUS

Ephedra Vulgaris 3xHPUS

Mezereum 3xHPUS

Petroleum 8xHPUS

Pulsatilla 3xHPUS

Thuja Occidentalis 10xHPUS

The letters HPUS indicates that the components in this product are officially monographed in the Homeopathic Pharmacopoeia of United States.

PURPOSE

For the temporary relief of sinus congestion due to colds and flu, hay fever, rhinitis, and nasal dryness.

Keep out of reach of children.

INDICATIONS AND USAGE

Adults: 1-2 sprays in each nostril as needed. Wipe tip clean after use. Not intended for infants or small children.

WARNINGS

Do not spray in eyes, mouth or ears.

If pregnant or breast-feeding, ask a health professional before use.

If swallowed, get medical help or contact Poison Control Center right away.

DOSAGE AND ADMINISTRATION

(Read INDICATIONS & USAGE SECTION)

INACTIVE INGREDIENT

Aqua Demineralisata; Aqua Hamamelidis; Alcohol 7.7% by volume, Glycerin and Thymol.